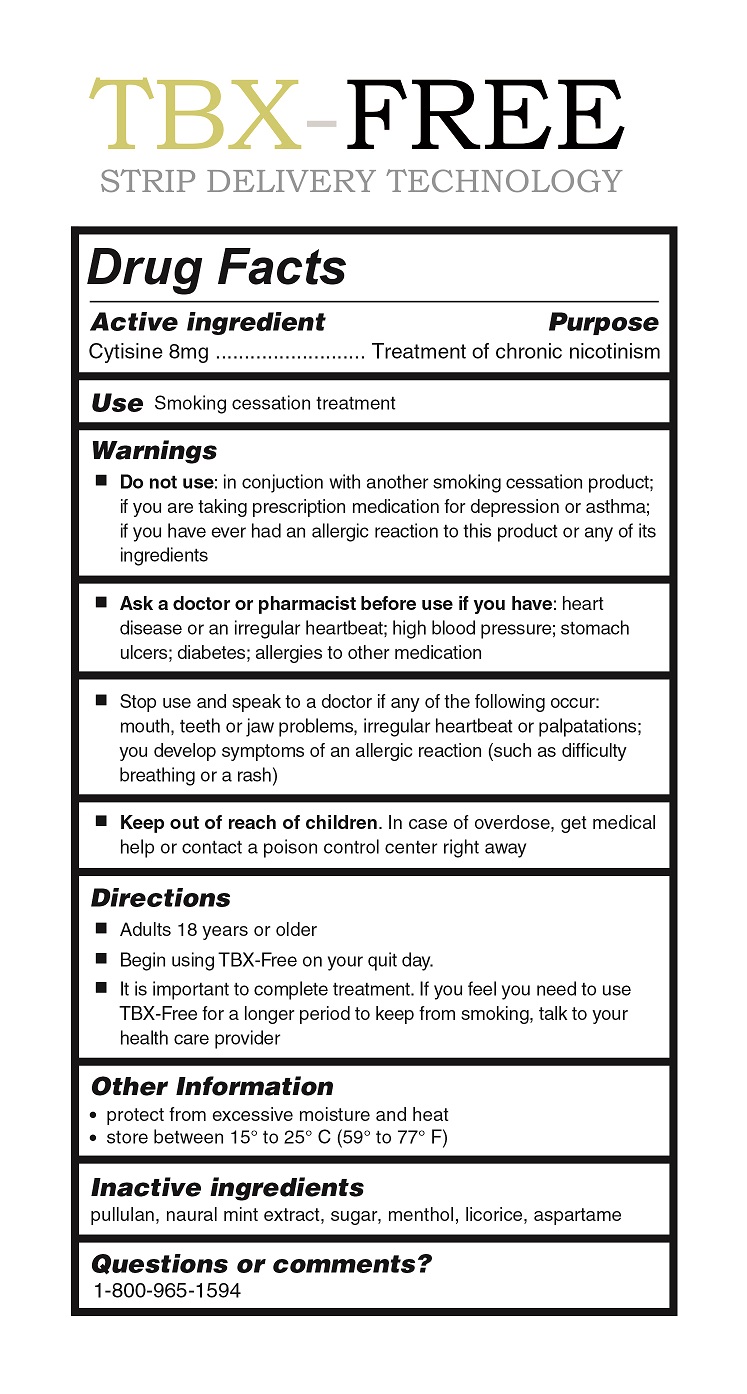 DRUG LABEL: TBX-Free
NDC: 69461-001 | Form: STRIP
Manufacturer: Dalian Jixin Electronic Information Co., Ltd.
Category: homeopathic | Type: HUMAN OTC DRUG LABEL
Date: 20151120

ACTIVE INGREDIENTS: CYTISINE 8 mg/1 mg
INACTIVE INGREDIENTS: SUCROSE; MENTHOL; LICORICE; PULLULAN; MINT; ASPARTAME

Active Ingredient

Cytisine 8mg

Purpose
Treatment of chronic nicotinism

KEEP OUT OF REACH OF CHILDREN

In case of overdose, get medical help or contact a poison control center right away.

Use
Smoking cessation treatment

DIRECTIONS

Adults 18 years or over

Begin using TBX-Free on your quit day

It is important to complete treatment. If you feel you need to use TBX-Free to keep from smoking, talk to your health care provider.

Warnings
Do not use: in conjunction with another smoking cessation product; if you are taking prescription medication for depression or asthma; if you have ever had an allergic reaction to this product or any of its ingredients.
Ask a doctor or pharmacist before use if you have: heart disease or an irregular heartbeat; high blood pressure; stomach ulcers; diabetes; allergies to other medication
Stop use and speak to a doctor if any of the following occur: mouth, teeth, or jaw problems, irregular heartbeat or palpitations; you develop symptoms of an allergic reaction (such as difficulty breathing or a rash)

Inactive Ingredients
pullulan, natural mint extract, sugar, menthol, licorice, aspartame

OTHER SAETY INFORMATION

Protect from excessiv moisture and heat

Store between 15º and 25º C (59º to 77 º F)

QUESTIONS OR COMMENTS

1-800-965-1594